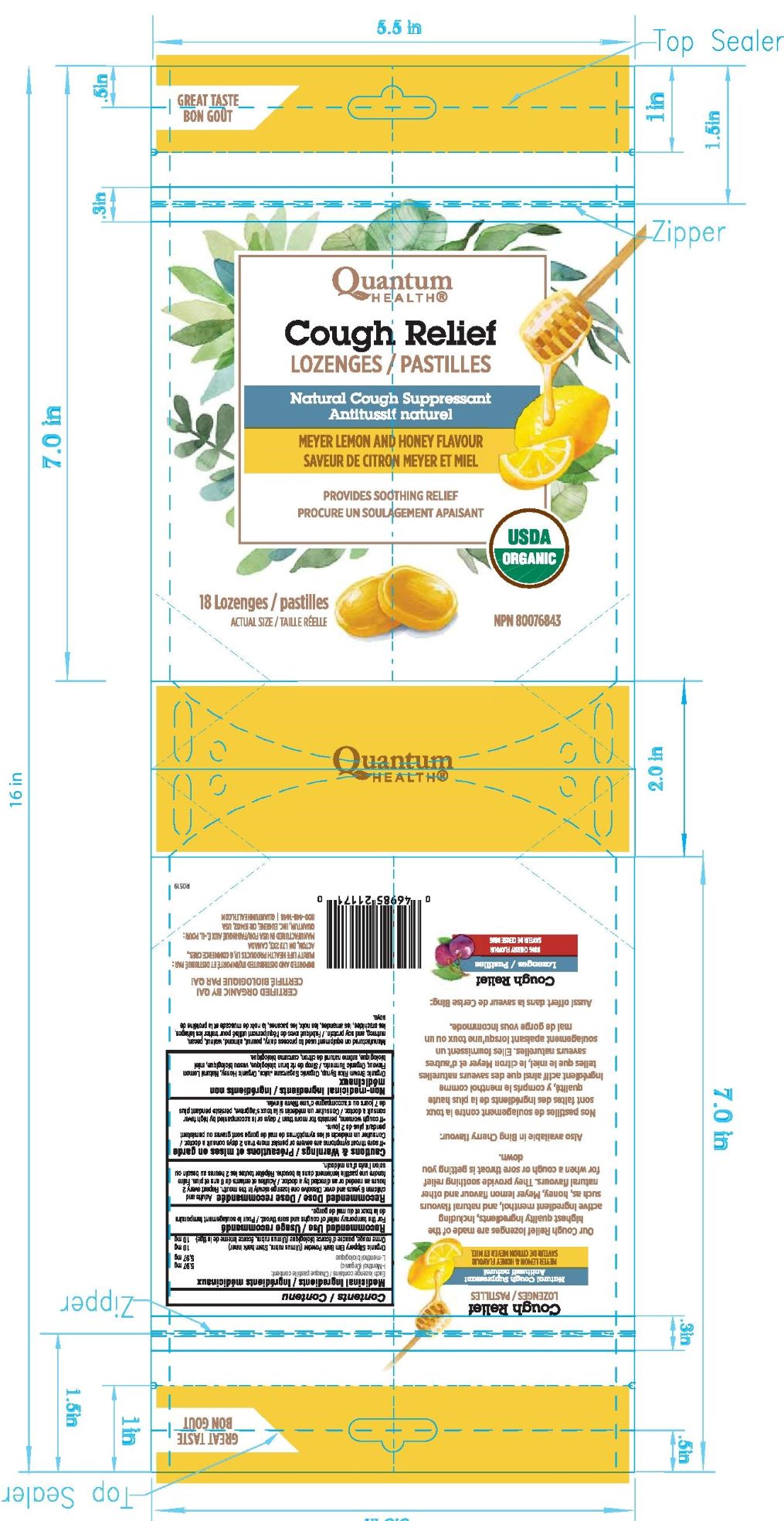 DRUG LABEL: Meyer Lemon and Honey-Cough Relief
NDC: 70084-613 | Form: LOZENGE
Manufacturer: Quantum Inc.
Category: otc | Type: HUMAN OTC DRUG LABEL
Date: 20200116

ACTIVE INGREDIENTS: MENTHOL 5.97 mg/1 1
INACTIVE INGREDIENTS: CURCUMA LONGA WHOLE; BARLEY MALT SYRUP; MEYER LEMON; ULMUS RUBRA BARK; SUGARCANE; HONEY

Meyer Lemon and Honey-Cough Relief Lozenges

ACTIVE INGREDIENT

Medicinal Ingredients:

Each lozenge contains:

l-Menthol 5.97mg

Organic Slippery Elm Bark Powder (Ulmus rubra, Stem bark inner) 10mg

INDICATIONS AND USAGE

Recommended Use

For the temporary relief of coughs and sore throat.

DOSAGE AND ADMINISTRATION

Recommended Dose

Adults and children 6 years and over. Dissolve one lozenge slowly in the mouth. Repeat every 2 hours as needed or as directed by a doctor.

Cautions & Warnings:

- If sore throat symptoms are severe or persist more than 2 days consult a doctor.

- If cough worsens, persists for more than 7 days or is accompanied by high fever consult a doctor.

INACTIVE INGREDIENT

Non-medicinal Ingredients

Organic Brown Rice Syrup, Organic Sugarcane juice, Organic Honey, Natural Lemon Flavour, Organic Tumeric

PURPOSE

Antitussif

Keep out of reach children